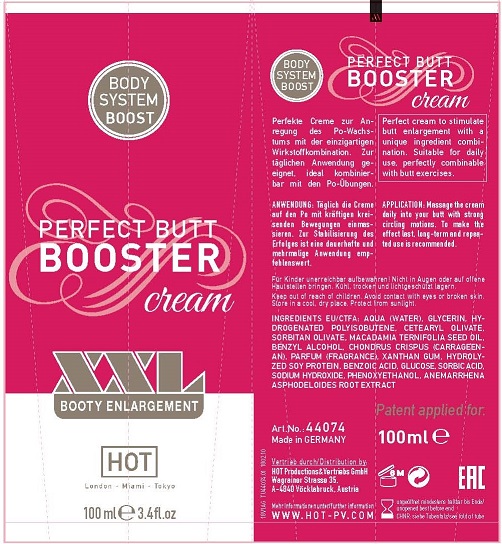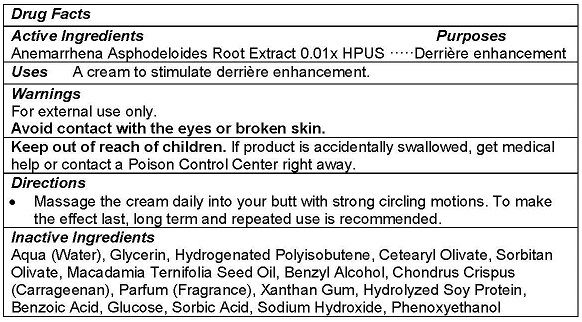 DRUG LABEL: PERFECT BUTT BOOSTER
NDC: 71326-302 | Form: CREAM
Manufacturer: HOT PRODUCTIONS AND VERTRIEBS GMBH
Category: homeopathic | Type: HUMAN OTC DRUG LABEL
Date: 20231005

ACTIVE INGREDIENTS: ANEMARRHENA ASPHODELOIDES ROOT 0.1 g/100 mL
INACTIVE INGREDIENTS: WATER; HYDROGENATED POLYBUTENE (1300 MW); GLYCERIN; CETEARYL OLIVATE; SORBITAN OLIVATE; MACADAMIA OIL; BENZYL ALCOHOL; CHONDRUS CRISPUS CARRAGEENAN; XANTHAN GUM; HYDROLYZED SOY PROTEIN (ENZYMATIC; 2000 MW); BENZOIC ACID; DEXTROSE, UNSPECIFIED FORM; SORBIC ACID; SODIUM HYDROXIDE; PHENOXYETHANOL

HOT PRODUCTS - Perfect Butt Booster Cream (71326-302)

ACTIVE INGREDIENTS

Anemarrhena Asphodeloides 0.1x HPUS

PURPOSE

Derrière care

USE

A cream to stimulate derrière enhancement.

WARNINGS

For external use only.
Avoid contact with the eyes or broken skin.

Keep out of reach of children. If product is accidentally swallowed, get medical help or contact a Poison Control Center right away.

DIRECTIONS

- Massage the cream daily into your butt with strong circling motions. To make the effect last, long term and repeated use is recommended.

INACTIVE INGREDIENTS

Aqua (Water), Glycerin, Hydrogenated Polyisobutene, Cetearyl Olivate, Sorbitan Olivate, Macadamia Ternifolia Seed Oil, Benzyl Alcohol, Chondrus Crispus (Carrageenan), Parfum (Fragrance), Xanthan Gum, Hydrolyzed Soy Protein, Benzoic Acid, Glucose, Sorbic Acid, Sodium Hydroxide, Phenoxyethanol